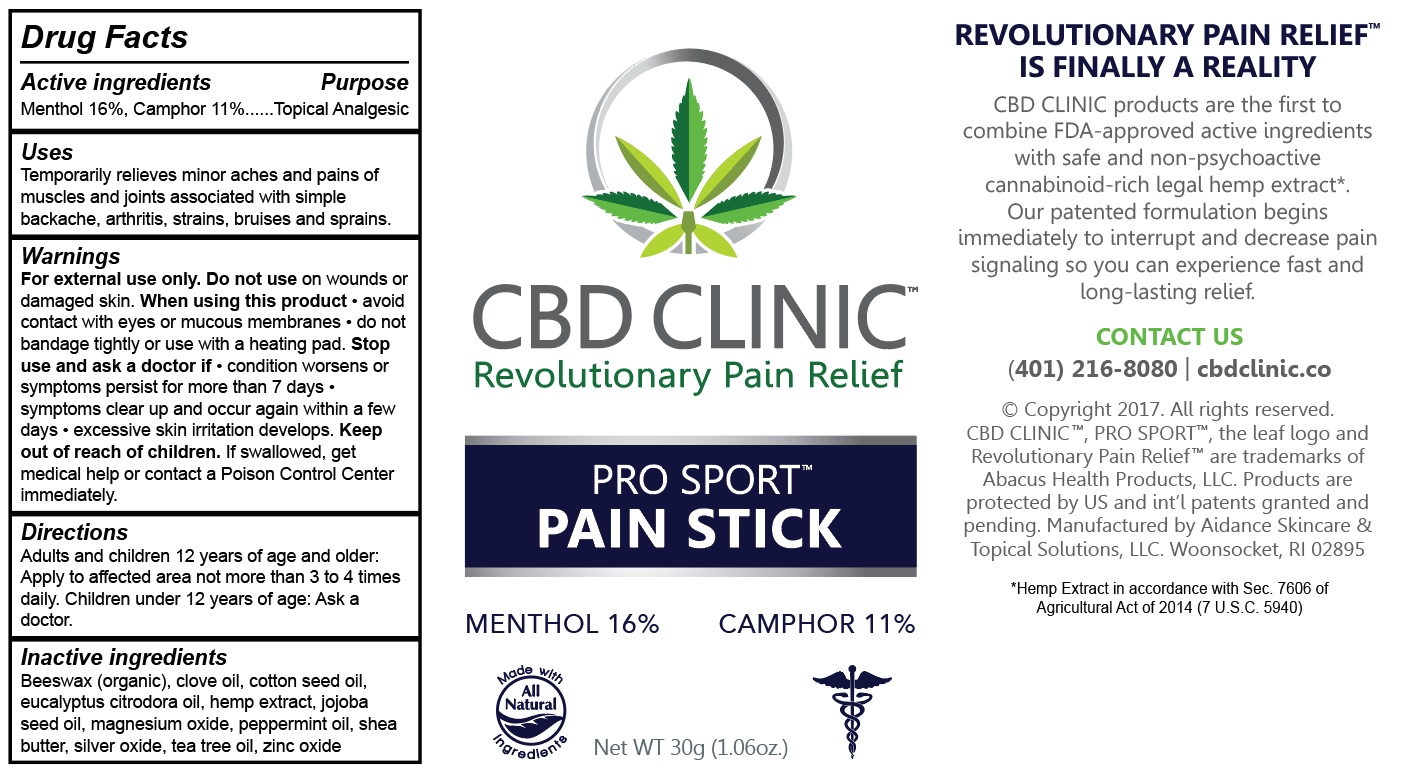 DRUG LABEL: CBD Clinic Pro Sport - Pain Stick
NDC: 24909-706 | Form: STICK
Manufacturer: Aidance Skincare & Topical Solutions, LLC
Category: otc | Type: HUMAN OTC DRUG LABEL
Date: 20171207

ACTIVE INGREDIENTS: MENTHOL 16 g/100 g; CAMPHOR (SYNTHETIC) 11 g/100 g
INACTIVE INGREDIENTS: CLOVE OIL; COTTONSEED OIL; EUCALYPTUS OIL; HEMP; JOJOBA OIL; MAGNESIUM OXIDE; PEPPERMINT OIL; SHEA BUTTER; SILVER OXIDE; TEA TREE OIL; WHITE WAX; ZINC OXIDE

Drug Facts

Active Ingredients

Menthol 16%, Camphor 11%

Purpose

Menthol, Camphor - Topical Analgesic

Uses

Temporarily relieves minor aches and pains of muscles and joints associated with simple backache, arthritis, strains, bruises and sprains.

Warnings

For external use only. Do not use on wounds or damaged skin. When using this product - avoid contact with eyes or mucous membranes - do not bandage tightly or use with heating pad. Stop use and ask a doctor if - condition worsens or symptoms persist for more than 7 days - symptoms clear up and occur again within a few days - excessive skin irritation develops.

Keep out of reach of children.

If swallowed, get medical help or contact a Poison Control Center immediately.

Directions

Adults and children 12 years of age and older: Apply to affected area not more than 3 to 4 times daily. Children under 12 years of age: Ask a doctor.

Inactive Ingredients

Beeswax (organic), hemp extract, clove oil, cotton seed oil, eucalyptus citrodora oil, jojoba seed oil, magnesium oxide, peppermint oil, shea butter, silver oxide, tea tree oil, zinc oxide.

PRINCIPAL DISPLAY PANEL - 30g Label

CBD CLINIC

Revolutionary Pain Relief
PRO SPORT™
PAIN STICK
MENTHOL 16% CAMPHOR 11%

Net WT 30g (1.06oz)